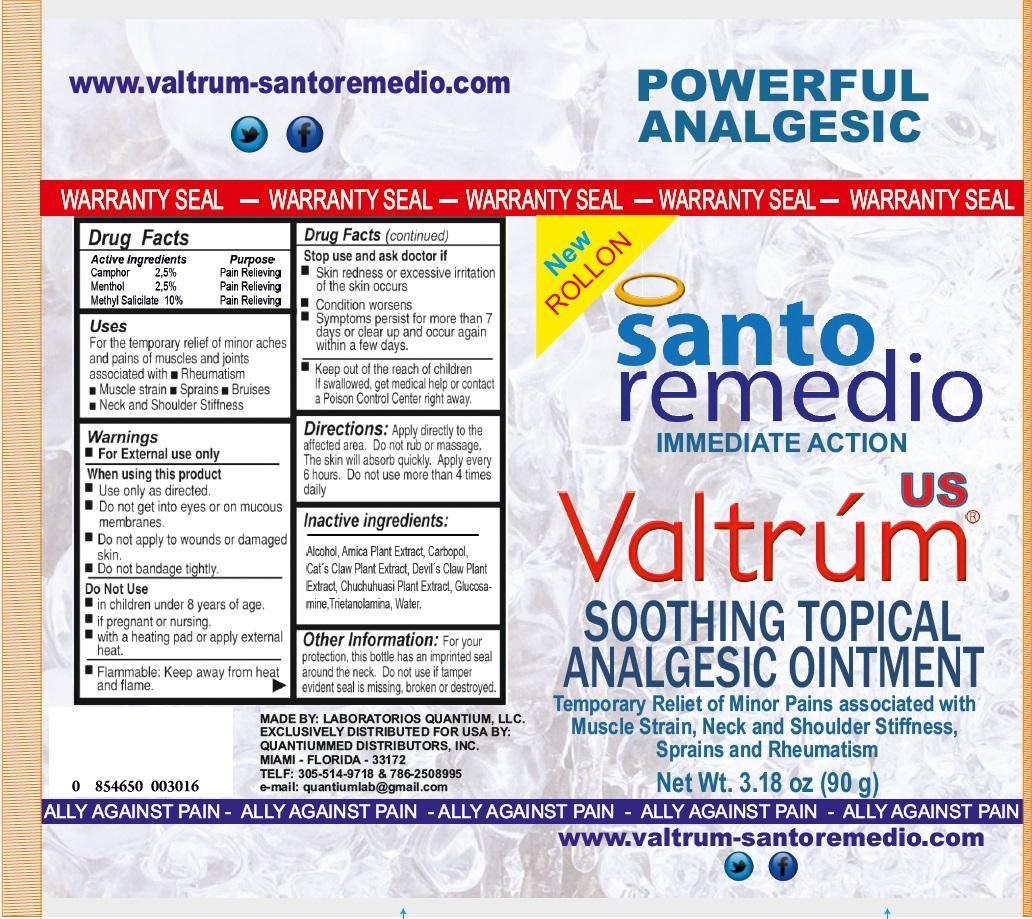 DRUG LABEL: Valtrum Soothing Topical Analgesic
NDC: 75849-300 | Form: OINTMENT
Manufacturer: Laboratorios Quantium LLC
Category: otc | Type: HUMAN OTC DRUG LABEL
Date: 20200928

ACTIVE INGREDIENTS: CAMPHOR (SYNTHETIC) 25 mg/1 g; MENTHOL 25 mg/1 g; METHYL SALICYLATE 100 mg/1 g
INACTIVE INGREDIENTS: ALCOHOL; HARPAGOPHYTUM PROCUMBENS ROOT; GLUCOSAMINE; TROLAMINE; WATER

Valtrum Soothing Topical Analgesic Ointment

Active Ingredients

Camphor 2,5%

Menthol 2,5%

Methyl Salicilate 10%

Purpose

Pain Relieving

Uses

For the temporary relief of minor aches and pains of muscles and joints associated with •Rheumatism •Muscle strain •Sprains •Bruises •Neck and Shoulder Stiffness

Warnings

- For External use only

When using this product

- Use only as directed.
- Do not get into eyes or on mucous membranes.
- Do not apply to wounds or damaged skin.
- Do not bandage tightly.

Do Not Use

- in children under 8 years of age.
- if pregnant or nursing.
- with heating pad or apply external heat.

Flammable:

- Keep away from heat and flame.

Stop use and ask doctor if

- Skin redness or excessive irritation of the skin occurs
- Condition worsens
- Symptoms persist for more than 7 days or clear up and occur again within a few days.

Keep out of the reach of children

If swallowed, get medical help or contact a Poison Control Center right away.

Directions:

Apply directly to the affected area. Do not rub or massage. The skin will absorb quickly. Apply every 6 hours. Do not use more than 4 times daily

Inactive ingredients:

Alcohol, Arnica Plant Extract, Carbopol, Cat's Claw Plant Extract, Devil's Claw Plant Extract, Chuchuhuasi Plant Extract, Glucosamine, Trietanolamina, water.

Other Information:

For your protection, this bottle has an imprinted seal around the neck. Do not use if tamper evident seal is missing, broken or destroyed.